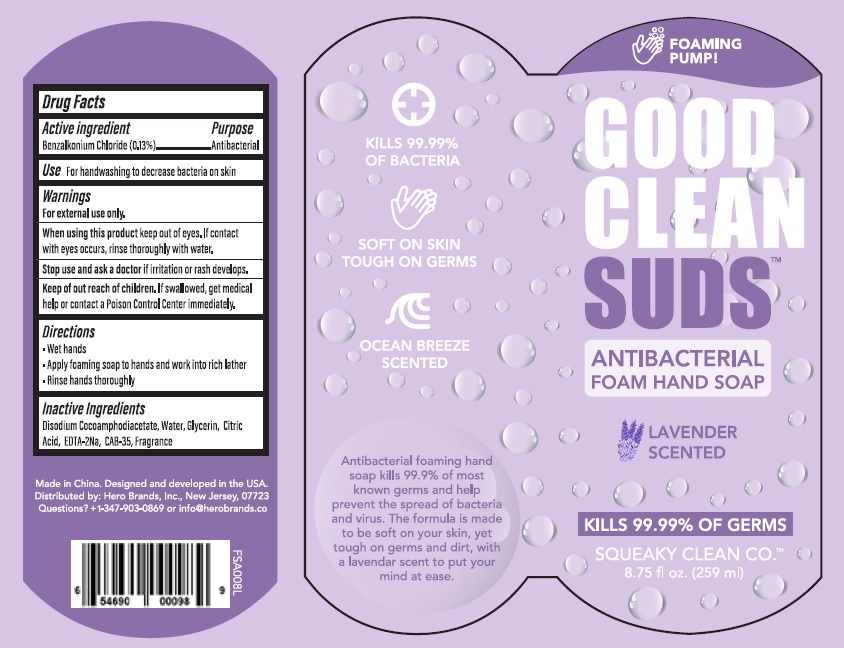 DRUG LABEL: Good Clean SUDS Antibacterial Foam Hand Lavender Scented
NDC: 75183-106 | Form: SOAP
Manufacturer: Zorin Pharmaceutical Technology (Hangzhou) Co Ltd.
Category: otc | Type: HUMAN OTC DRUG LABEL
Date: 20201123

ACTIVE INGREDIENTS: BENZALKONIUM CHLORIDE 1.3 mg/1 mL
INACTIVE INGREDIENTS: WATER; GLYCERIN; DISODIUM COCOAMPHODIACETATE; ANHYDROUS TRISODIUM CITRATE

Active ingredient

Benzalkonium Chloride ................. 0.13%

Purpose

Antibacterial

USE

For handwashing to decrease bacteria on skin.

Warnings

For external use only.

When using this product

keep out of eyes, if contact with eyes occurs, rinse thoroughly with water.

Stop use and ask a doctor

if irritation and rash develops.

Keep out of reach of children.

If swallowed, get medical help or contact a Poison Control Center immediately.

Directions

- Wet hands
- Apply foaming soap to hands and work into rich lather.
- Rinse hands thoroughly.

Inactive ingredients

Disodium Cocoamphodiacetate, Water, Glycerin, Citric Acid, EDTA-2Na, CAB-35, Fragrance